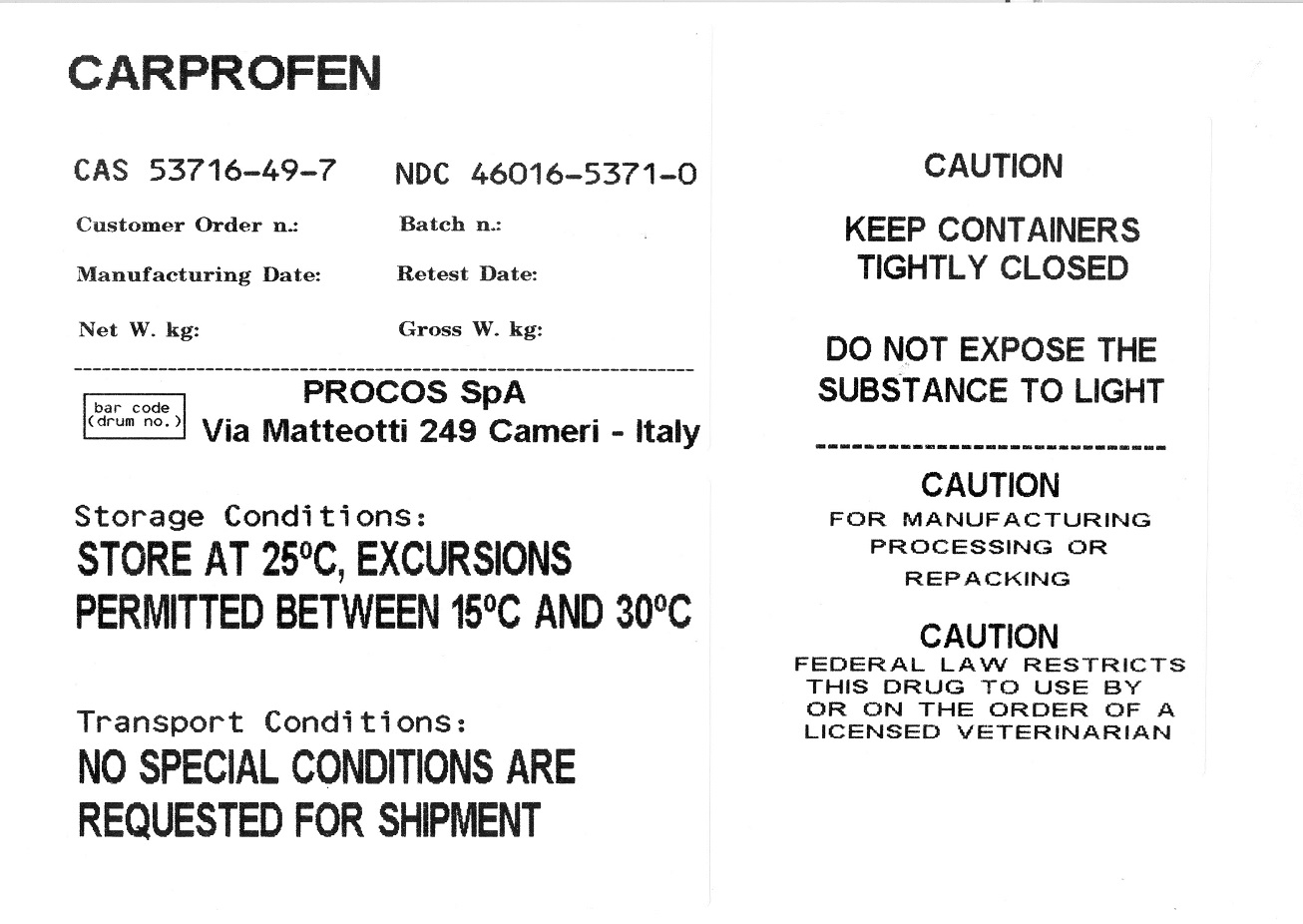 DRUG LABEL: CARPROFEN
NDC: 46016-5371 | Form: POWDER
Manufacturer: PROCOS SpA
Category: other | Type: BULK INGREDIENT - ANIMAL DRUG
Date: 20211007

ACTIVE INGREDIENTS: CARPROFEN 50 kg/50 kg

CARPROFEN

PACKAGE LABEL

CARPROFEN

CAS 53716-49-7

NDC 46016-5371-0

PROCOS SpA

Via Matteotti 249 Cameri - Italy

Storage Conditions:

STORE AT 25°C, EXCURSIONS PERMITTED BETWEEN 15°C AND 30°C

Transport Conditions:

NO SPECIAL CONDITIONS ARE REQUESTED FOR SHIPMENT

CAUTION

KEEP CONTAINERS TIGHTLY CLOSED

DO NOT EXPOSE THE SUBSTANCE TO LIGHT

CAUTION

FOR MANUFACTURING PROCESSING OR REPACKING

CAUTION

FEDERAL LAW RESTRICTS THIS DRUG TO USE BY OR ON THE ORDER OF A LICENSED VETERINARIAN